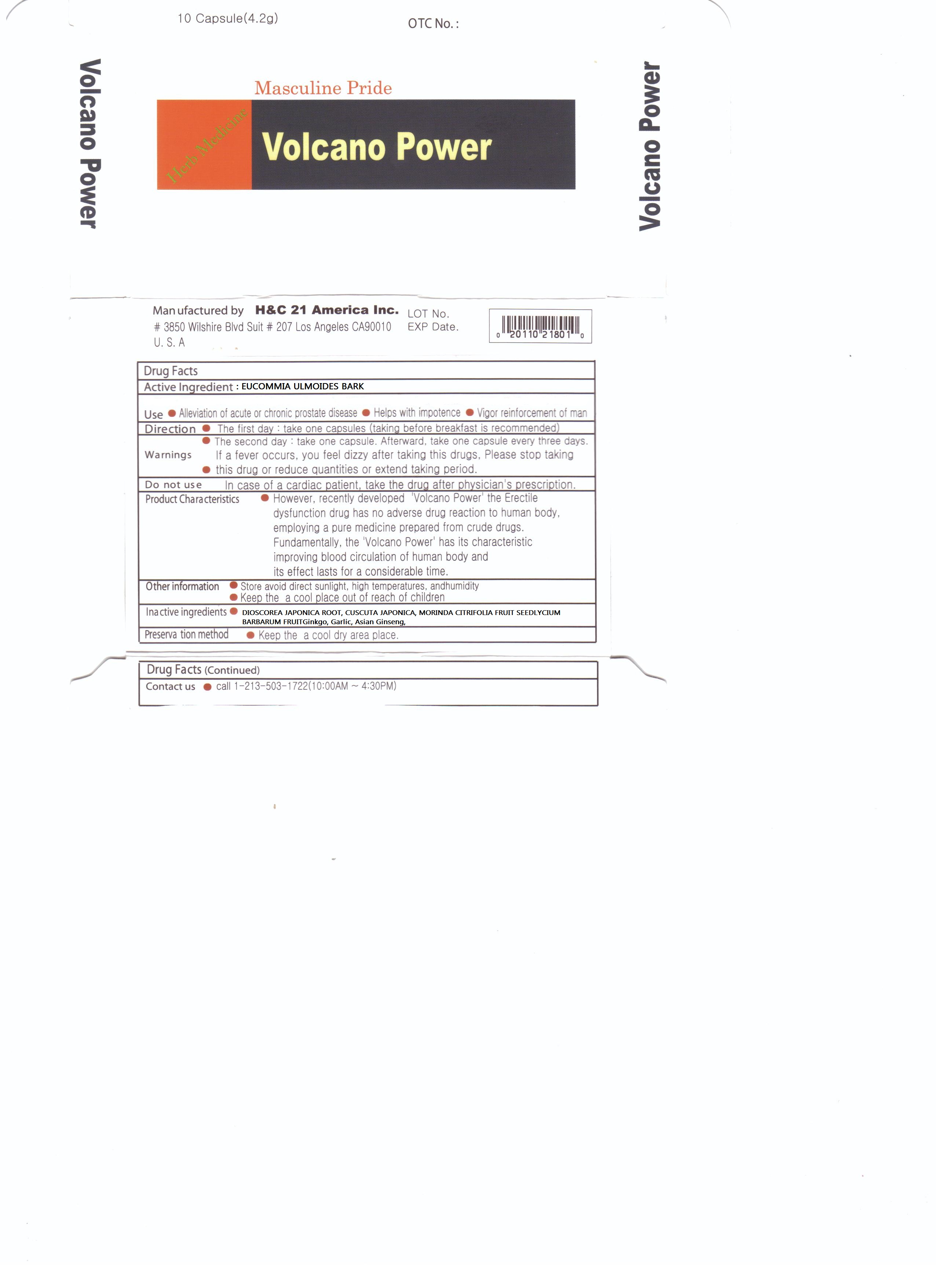 DRUG LABEL: Volcano Power
NDC: 76255-1001 | Form: CAPSULE
Manufacturer: H&C 21 America Inc
Category: otc | Type: HUMAN OTC DRUG LABEL
Date: 20110611

ACTIVE INGREDIENTS: EUCOMMIA ULMOIDES BARK 54 mg/1 1
INACTIVE INGREDIENTS: DIOSCOREA JAPONICA ROOT; GARLIC; GINKGO; ASIAN GINSENG; LYCIUM BARBARUM FRUIT; CUSCUTA JAPONICA SEED; MORINDA CITRIFOLIA FRUIT

Drug Facts

active ingredient: eucommia ulmoides

inactive ingredient: disocorea japonica, discorea batatsa, garlic lawn grass liripe muscari, chaenemeles laponical, ginkgo bilova, cordyceps militaris, red ginseng, schizandra, chinese, matrimony vine, cuscuta seed, rubus coreanus fruit, cnidii fructus, morinda citrfldia

PURPOSE

alleviation of acute or chronic prostate disease
helps with impotence
vigor reinforcement of man

keep out of reach of the children

INDICATIONS AND USAGE

- the first day: take one capsule, afterward take one capsule every three days

WARNINGS

if a fever occurs or feel dizzy after taking this drugs, please stop taking

DOSAGE AND ADMINISTRATION

reduce quantities or extend taking period